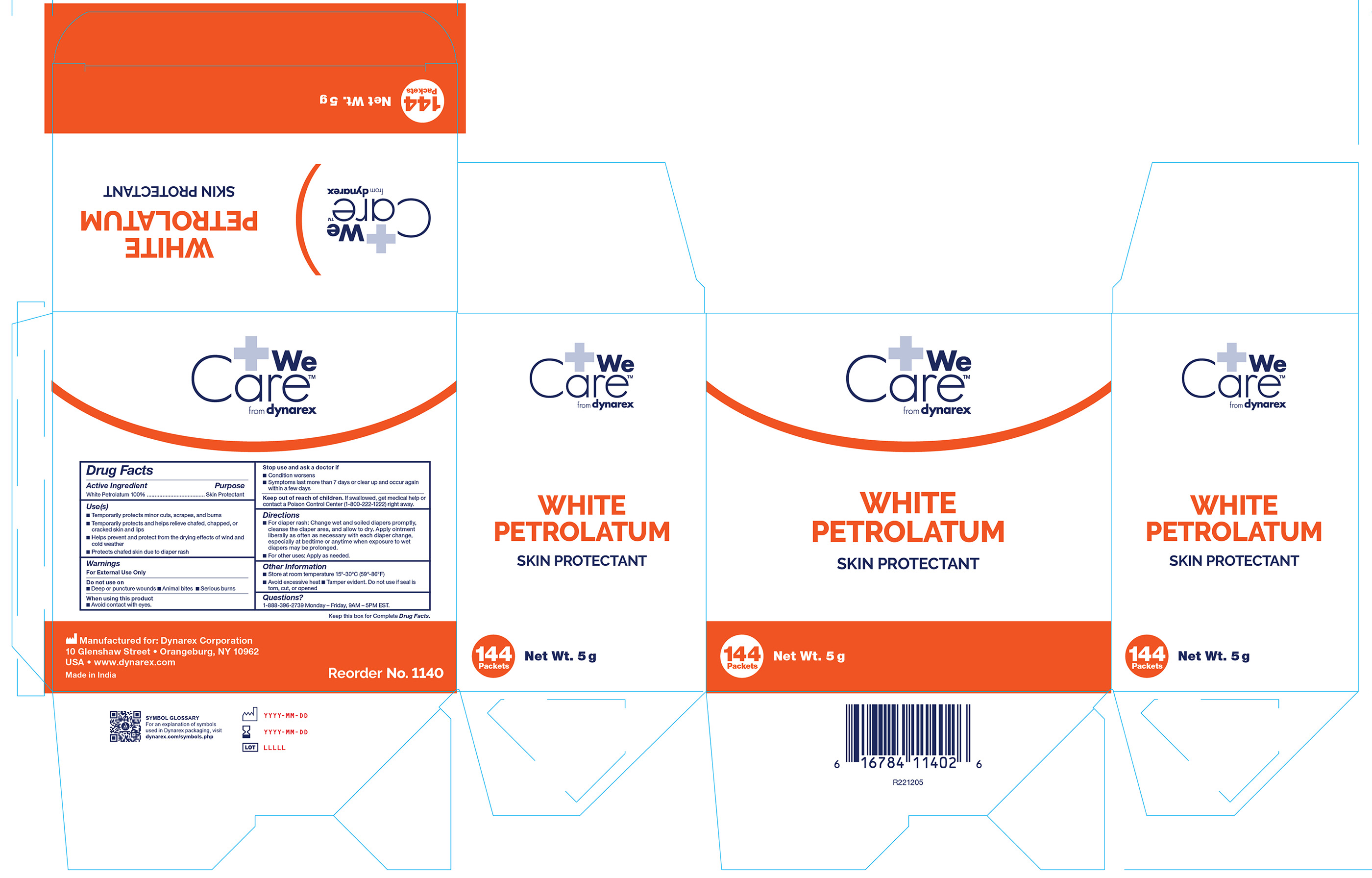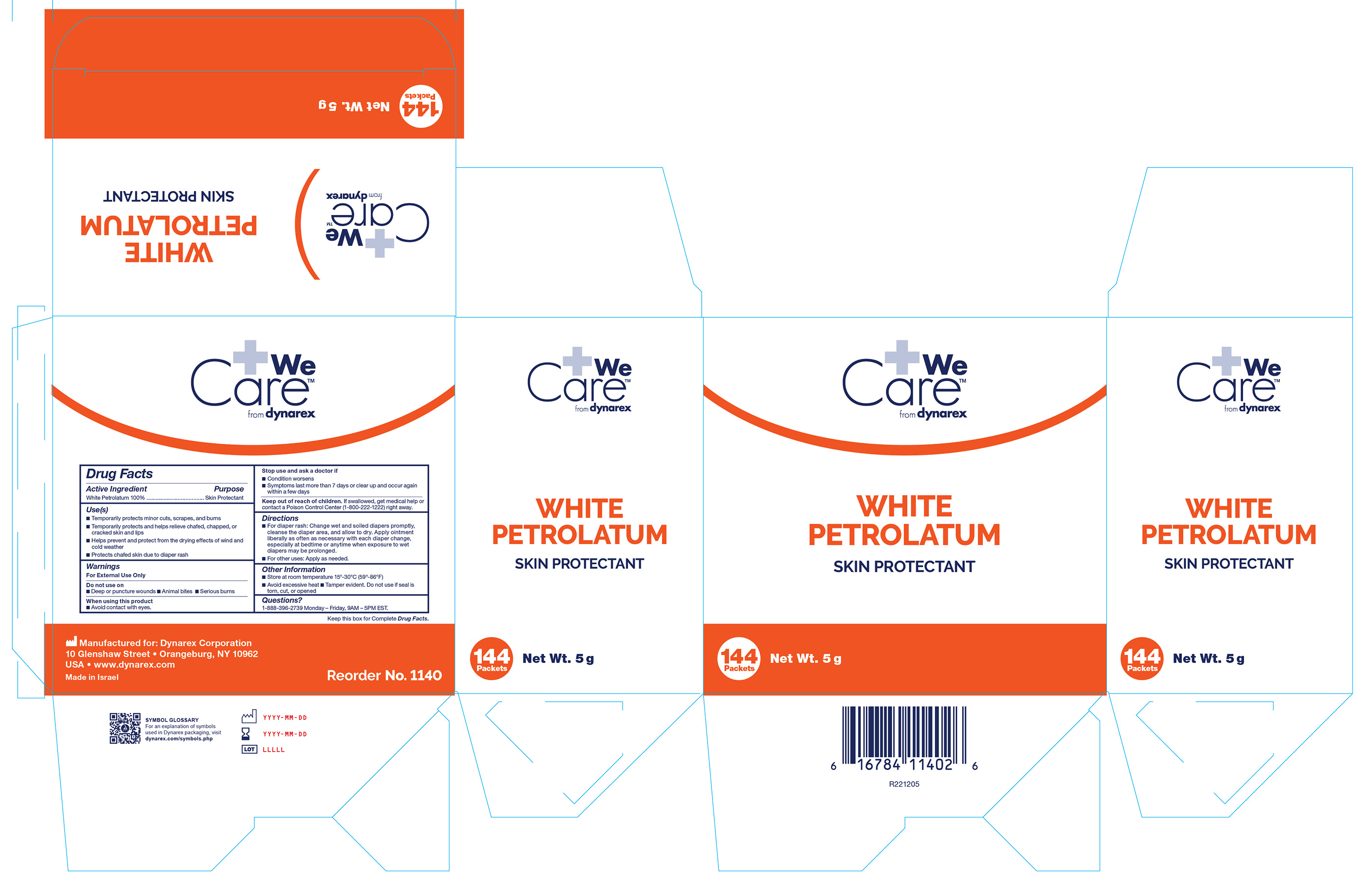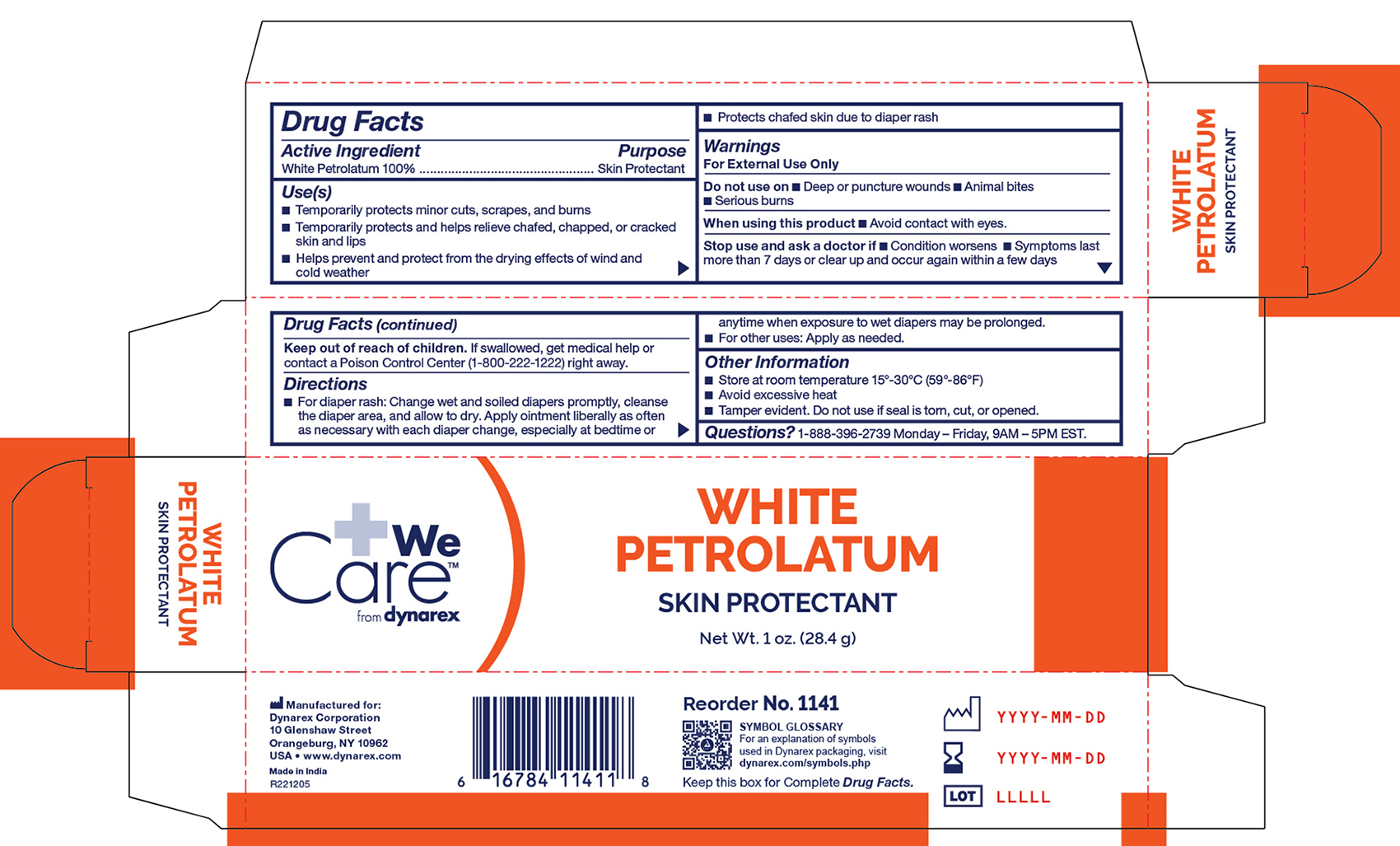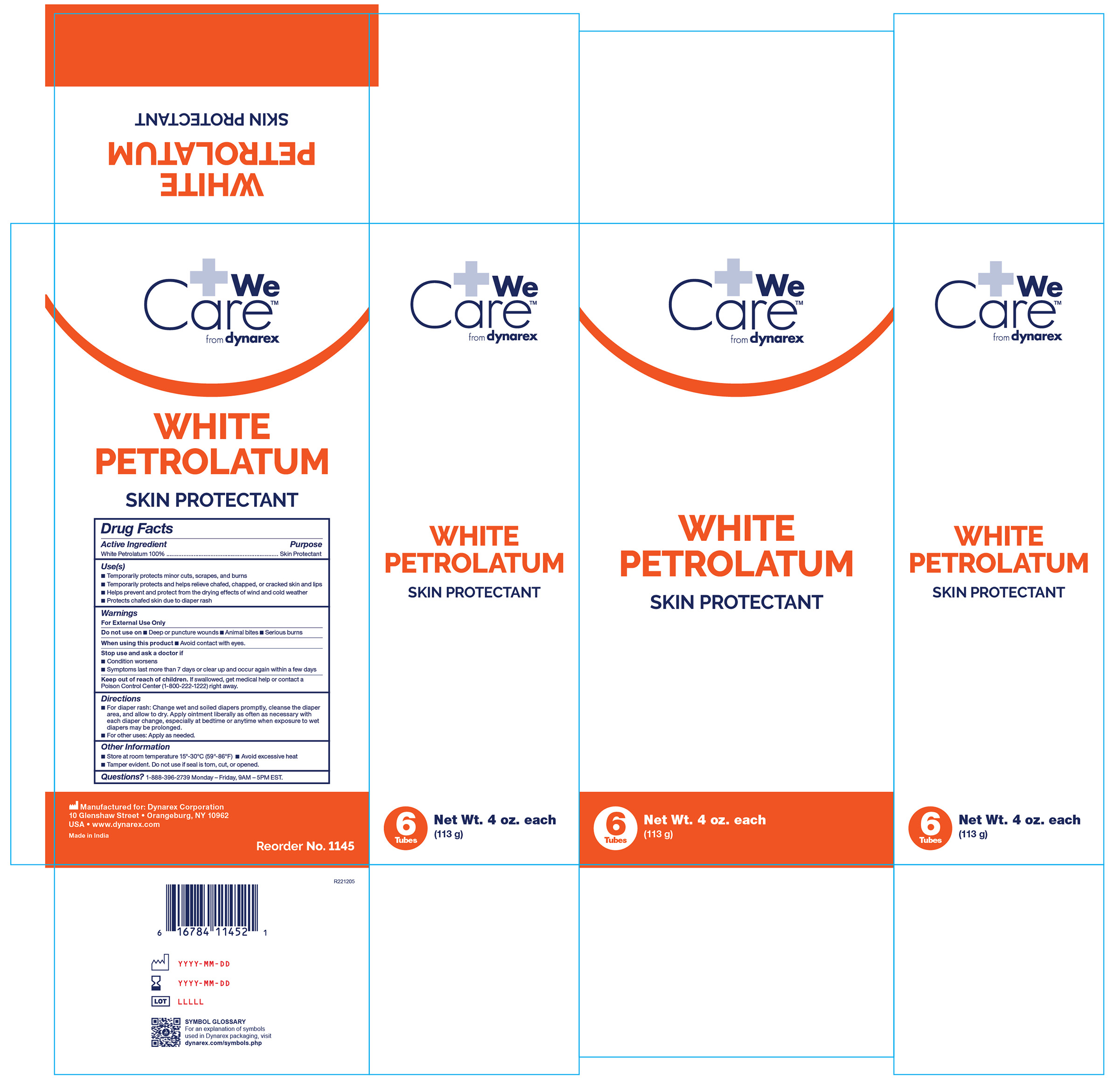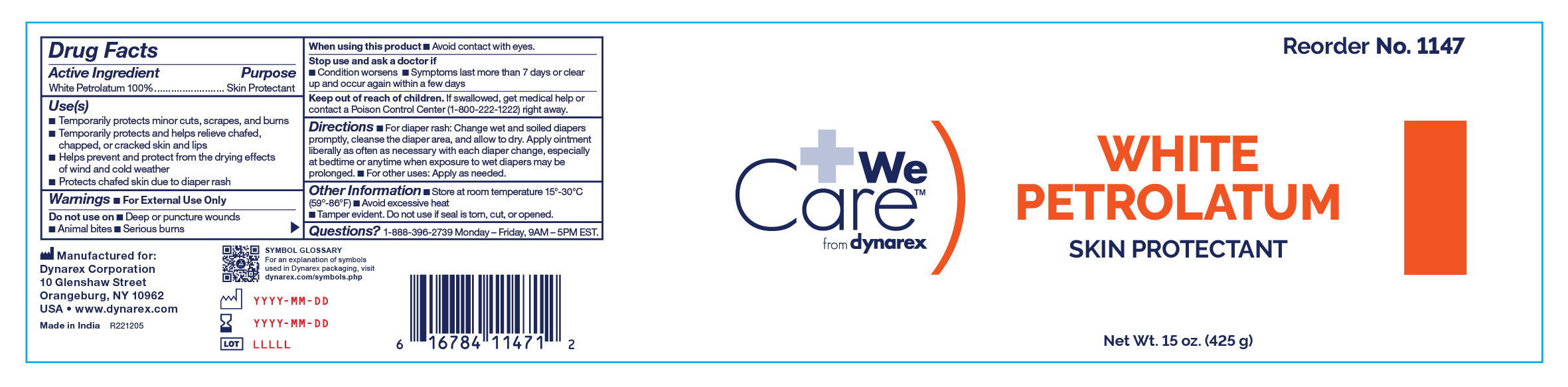 DRUG LABEL: White Petrolatum
NDC: 67777-005 | Form: OINTMENT
Manufacturer: Dynarex Corporation
Category: otc | Type: HUMAN OTC DRUG LABEL
Date: 20260122

ACTIVE INGREDIENTS: WHITE PETROLATUM 1 g/1 g

1140 White Petrolatum NDC 67777-005-00
1141 White Petrolatum NDC 67777-005-10
1145 White Petrolatum NDC 67777-005-50
1147 White Petrolatum NDC 67777-005-70

Active Ingredient

White Petrolatum 100%

Purpose

Skin Protectant

Uses

• Temporarily protects minor cuts, scrapes, burns

• Temporarily protects and helps relieve chafed, chapped, or cracked skin and lips

• Helps prevent and protect from the drying effects of wind and cold weather

• Protects chafed skin due to diaper rash

Warnings

For external use only

Do not use on

• Deep or puncture wounds

• Animal bites

• Serious burns

When using this product

• Avoid contact with eyes

Stop use and ask a doctor if

• Condition worsens

• Symptoms last more than 7 days or clear up and occur again within a few days

Keep out of reach of children.

If swallowed, get medical help or contact a Poison Control Center (1-800-222-12222) right away.

Directions

• For diaper rash: Change wet and soiled diapers promptly, cleanse the diaper area, and allow to dry. Apply ointment liberally as often as necessary with each diaper change, especially at bedtime or anytime when exposure to wet diapers may be prolonged.

• For other uses: Apply as needed.

Other Information

• Store at room temperature 15º-30ºC (59º-86ºF)

• Avoid excessive heat

• Tamper evident. Do not use if seal is torn, cut, or opened

Questions?

1-888-396-2739 Monday - Friday, 9AM - 5PM EST.

INACTIVE INGREDIENT

none

Label

1140 White Petrolatum

Label

1141 White Petrolatum

Label

1147 White Petrolatum

Label

1145 White Petrolatum